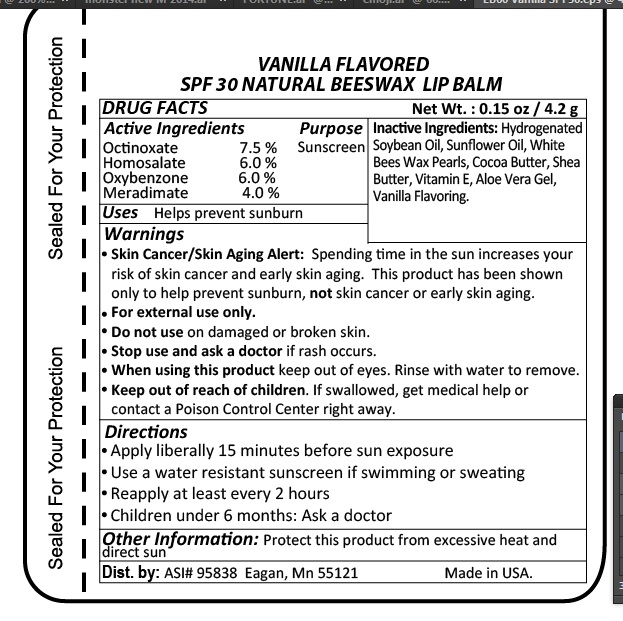 DRUG LABEL: Lip Balm Vanilla Flavored
NDC: 70445-165 | Form: LIPSTICK
Manufacturer: Webb Business Promotions
Category: otc | Type: HUMAN OTC DRUG LABEL
Date: 20220104

ACTIVE INGREDIENTS: HOMOSALATE 6 g/100 g; OCTINOXATE 7.5 g/100 g; OXYBENZONE 6 g/100 g; MERADIMATE 4 g/100 g
INACTIVE INGREDIENTS: WHITE WAX; SUNFLOWER OIL; HYDROGENATED SOYBEAN OIL; COCOA BUTTER; SHEA BUTTER; ALOE VERA LEAF; .ALPHA.-TOCOPHEROL

SPF 30 Vanilla Favored Lip Balm

Purpose

Sun Screen

Drug Facts

Octinoxate 7.5%

Homosalate 6.0%

Oxybenzone 6.0%

Meradimate 4.0%

Inactive Ingredients

Hydrogenated Soybean Oil, Sunflower Oil, Yellow Bees Wax Pearls, Cocoa Butter, Shea Butter, Vitamin E, Aloe Vera Gel, Bacon Flavoring

Warnings

- Skin Cancer/Skin Aging Alert: Spending too much time in the sun increases your risk of skin cancer and early skin aging. This product has been shown to only help prevent sunburn, not skin cancer or early skin aging.
- For external use only.
- Do not use on damaged or broken skin.
- Stop use and ask doctor if rash occurs.
- When using this product keep out of eyes.
- Keep out of reach of children. If swallowed get medical help or contact posion control center right away.

Directions

- Apply liberally 15 minutes before sun exposure
- Use a water resistant sunscreen if swimming or sweating
- Reapply every 2 hours
- Children under 6 months : Ask a doctor

Storage and Handling Information

Protect this product from excessive heat and direct sun